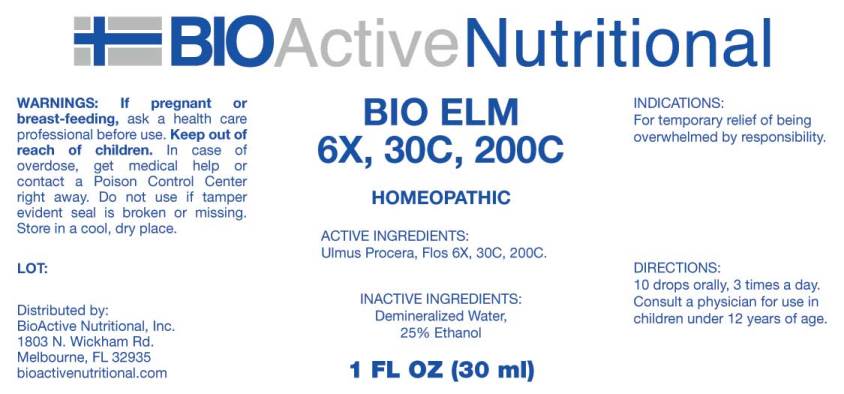 DRUG LABEL: Bio Elm
NDC: 43857-0178 | Form: LIQUID
Manufacturer: BioActive Nutritional, Inc.
Category: homeopathic | Type: HUMAN OTC DRUG LABEL
Date: 20180125

ACTIVE INGREDIENTS: ULMUS PROCERA FLOWERING TWIG 6 [hp_X]/1 mL
INACTIVE INGREDIENTS: WATER; ALCOHOL

Drug Facts:

ACTIVE INGREDIENTS:

Ulmus Procera, Flos 6X, 30C, 200C.

INDICATIONS:

For temporary relief of being overwhelmed by responsibility.

WARNINGS:

If pregnant or breast-feeding, ask a health care professional before use.

Keep out of reach of children. In case of overdose, get medical help or contact a Poison Control Center right away.

Do not use if tamper evident seal is broken or missing.

Store in cool, dry place.

DIRECTIONS:

10 drops orally, 3 times a day. Consult a physician for use in children under 12 years of age.

INACTIVE INGREDIENTS:

Demineralized Water, 25% Ethanol.

Keep out of reach of children. In case of overdose, get medical help or contact a Poison Control Center right away.

INDICATIONS:

For temporary relief of being overwhelmed by responsibility.

QUESTIONS:

Distributed by:

BioActive Nutritional, Inc.

1803 N. Wickham Rd.

Melbourne, FL 32935

bioactivenutritional.com

PACKAGE LABEL DISPLAY:

BIOActive Nutritional

BIO ELM

6X, 30C, 200C

1 FL OZ (30 ml)